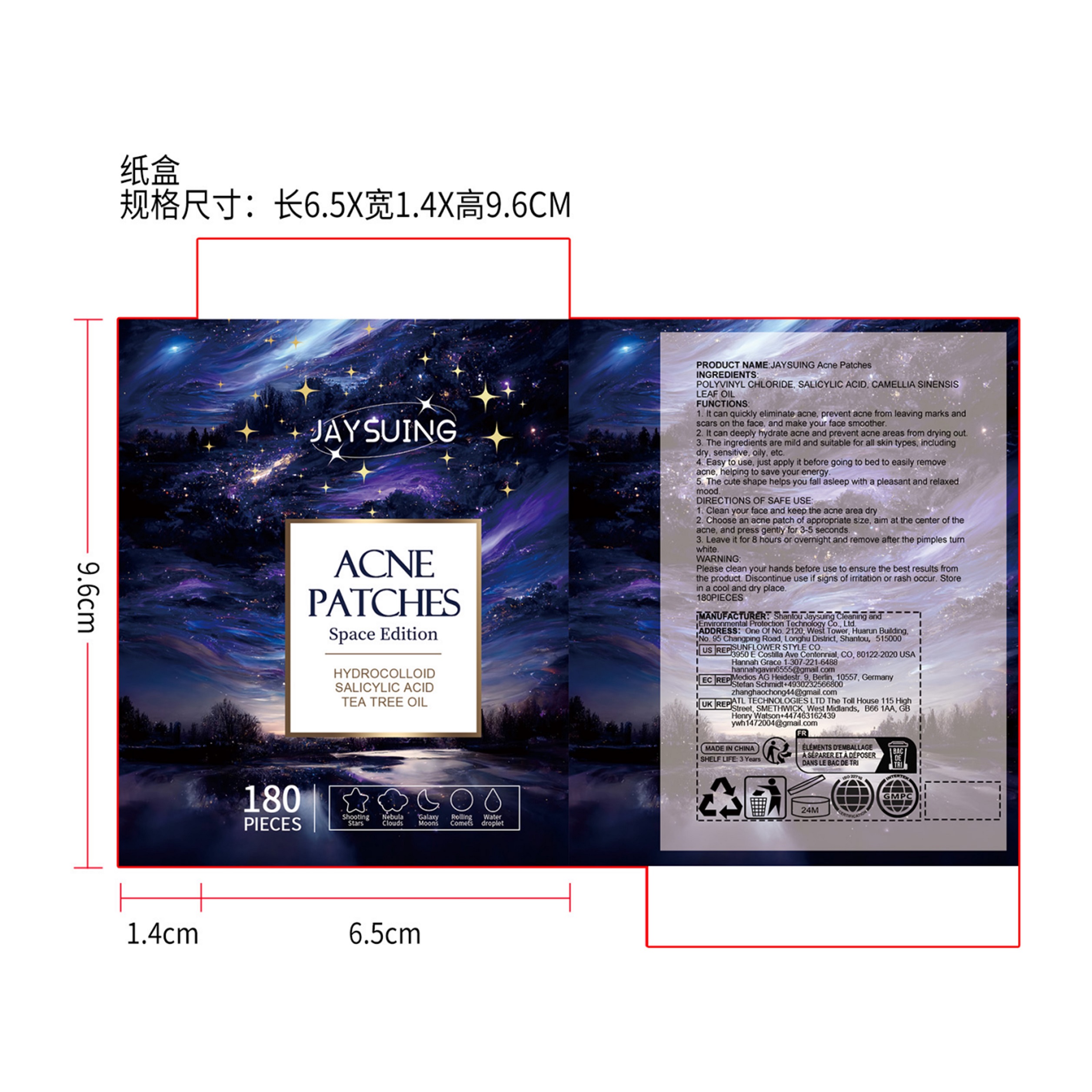 DRUG LABEL: JAYSUING ACNE PATCHES
NDC: 85060-001 | Form: PATCH
Manufacturer: Shantou Jaysuing Cleaning and Environmental Protection Technology Co., Ltd.
Category: otc | Type: HUMAN OTC DRUG LABEL
Date: 20251127

ACTIVE INGREDIENTS: SALICYLIC ACID 0.02 g/100 g
INACTIVE INGREDIENTS: POLYVINYL CHLORIDE K77; CAMELLIA SINENSIS LEAF OIL

Active Ingredient(s)

SAEICYLIC ACID

Purpose

1. it can quickly eliminate acne, prevent acne from leaving marks andscars on the face, and make your face smoother.

2. it can deeply hydrate acne and prevent acne areas from drying out

3. The ingredients are mild and suitable for all skin types, incudingdry,sensitive. oily. etc.

4. Easy to use, just apply it before going to bed to easily removeacne, helping to save your energy.

5 The cute shape helps you fall asleep with a pleasant and relaxedmood.

none

Warnings

Please clean your hands before use to ensure the best results fromthe product. Discontinue use if signs of irritation or rash occur. Storein a cool and dry place.

none

none

none

STORAGE AND HANDLING

Store om a cool and dry place

INACTIVE INGREDIENT

POLYVINYL CHLORIDE,,CAMELLIA SINENSIS LEAF OIL

DIRECTIONS OF SAFE USE:

1. Clean your face and keep the acne area dry

2. Choose an acne patch of appropriate size, aim at the center of theacne, and press gently for 3-5 seconds.

3. Leave it for 8 hours or overnight and remove after the pimples tumwhite.